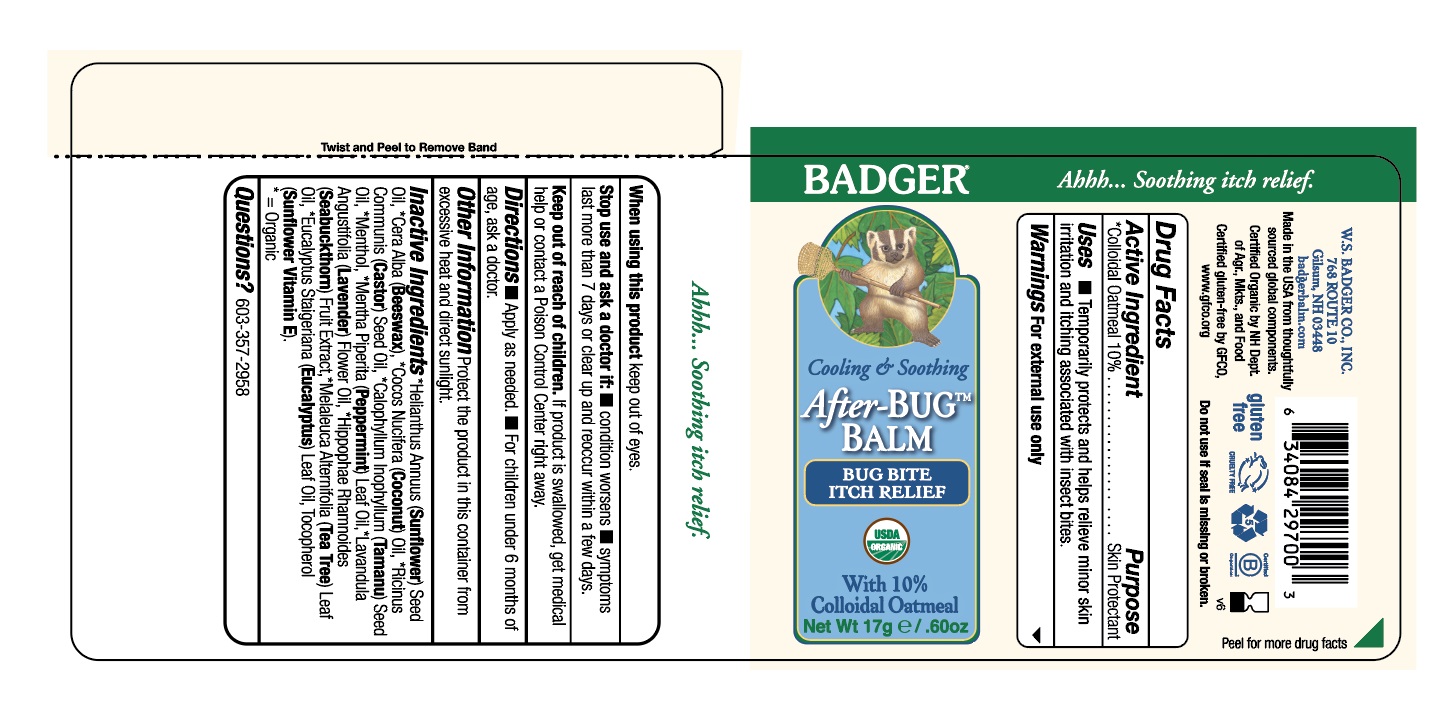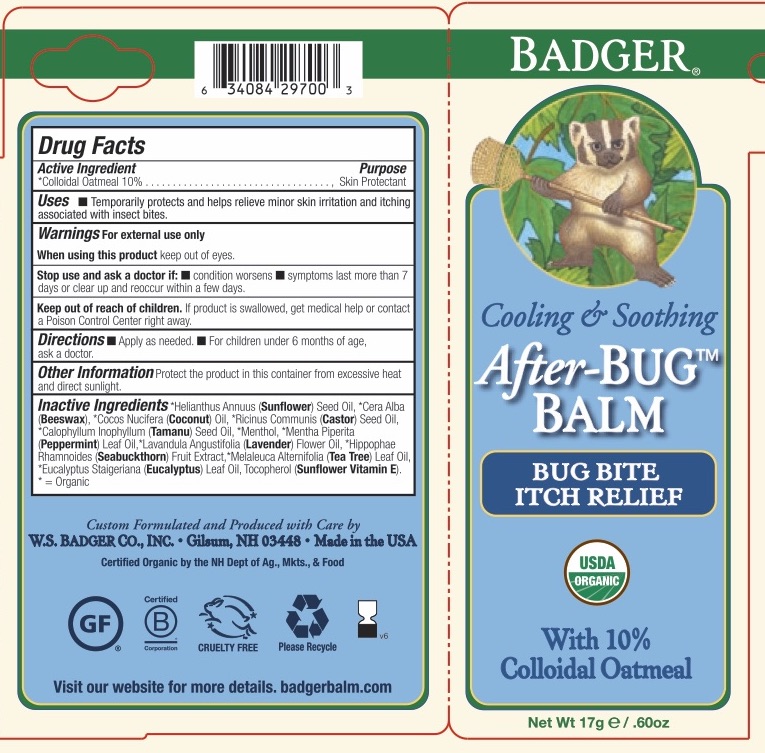 DRUG LABEL: Badger After-BUG Balm
NDC: 62206-0297 | Form: STICK
Manufacturer: W.S. Badger Company, Inc.
Category: otc | Type: HUMAN OTC DRUG LABEL
Date: 20211117

ACTIVE INGREDIENTS: OATMEAL 10 g/100 g
INACTIVE INGREDIENTS: MENTHOL; TEA TREE OIL; EUCALYPTUS OIL; CASTOR OIL; TAMANU OIL; PEPPERMINT OIL; LAVENDER OIL; HIPPOPHAE RHAMNOIDES FRUIT; SUNFLOWER OIL; YELLOW WAX; TOCOPHEROL; COCONUT OIL

Set EOM's; Badger® After-BUG Balm

Drug Facts

Active Ingredient

Colloidal Oatmeal 10%

Purpose

Skin Protectant

Uses

Uses • Temporarily protects and helps relieve minor skin irritation and itching associated with insect bites.

Warnings

For external use only

When using this product keep out of eyes.

Stop use and ask a doctor if

- condition worsens .
- symptoms last more than 7 days or clear up and reoccur within a few days.

Keep out of reach of children. If swallowed, get medical help or contact a poison control center right away.

Directions

- Apply as needed .
- For children under 6 months of age, ask a doctor.

Ingredients

[= Certified Organic] Helianthus Annuus (Sunflower) Oil, Cera Alba (Beeswax),^1Cocos Nuclfera (Coconut) Oil,^1Ricinus Communis (Castor) Seed Oil,^1Calophyllum Inophyllum (Tamanu) Seed Oil,^1Menthol, 'Mentha Piperita (Peppermint) Leaf Oil:^1Lavandula Anguslifolia (Lavender) Flower Oil,^1Hippophae Rhamnoides (Sea buckthorn) Fruit Extract,^1Melaleuca Alternifolia (Tea Tree) Leaf Oil,^1Eucalyptus Staigeriana (Eucalyptus) Leaf Oil, Tocopherol (Sunflower Vitamin E).

Other Information

Protect the product in this container from excessive heat and direct sunlight.

Questions?

(603) 357-2958

PRINCIPAL DISPLAY PANEL - 17g/.60 oz Label

BADGER®

Cooling & Soothing

After-BUG Balm

BUG BITE

ITCH RELIEF

USDA Organic

With 10%

Colloidal Oatmeal

17g/.60 oz